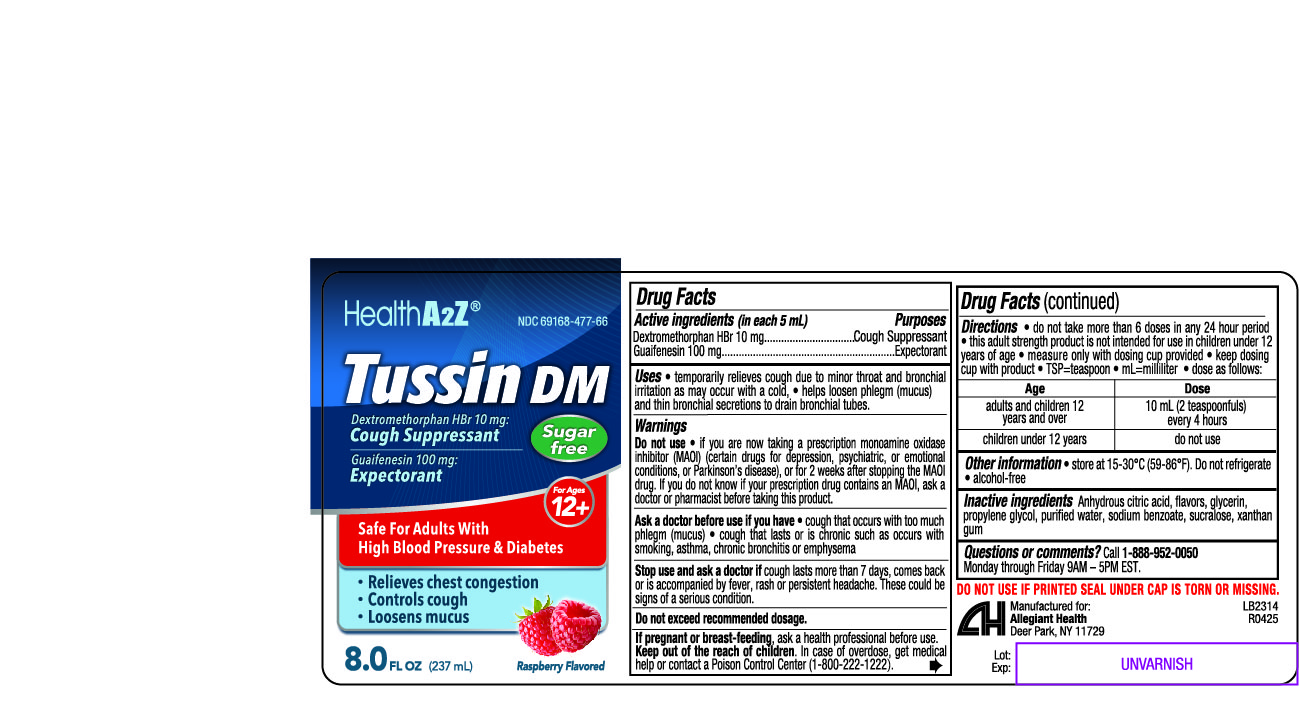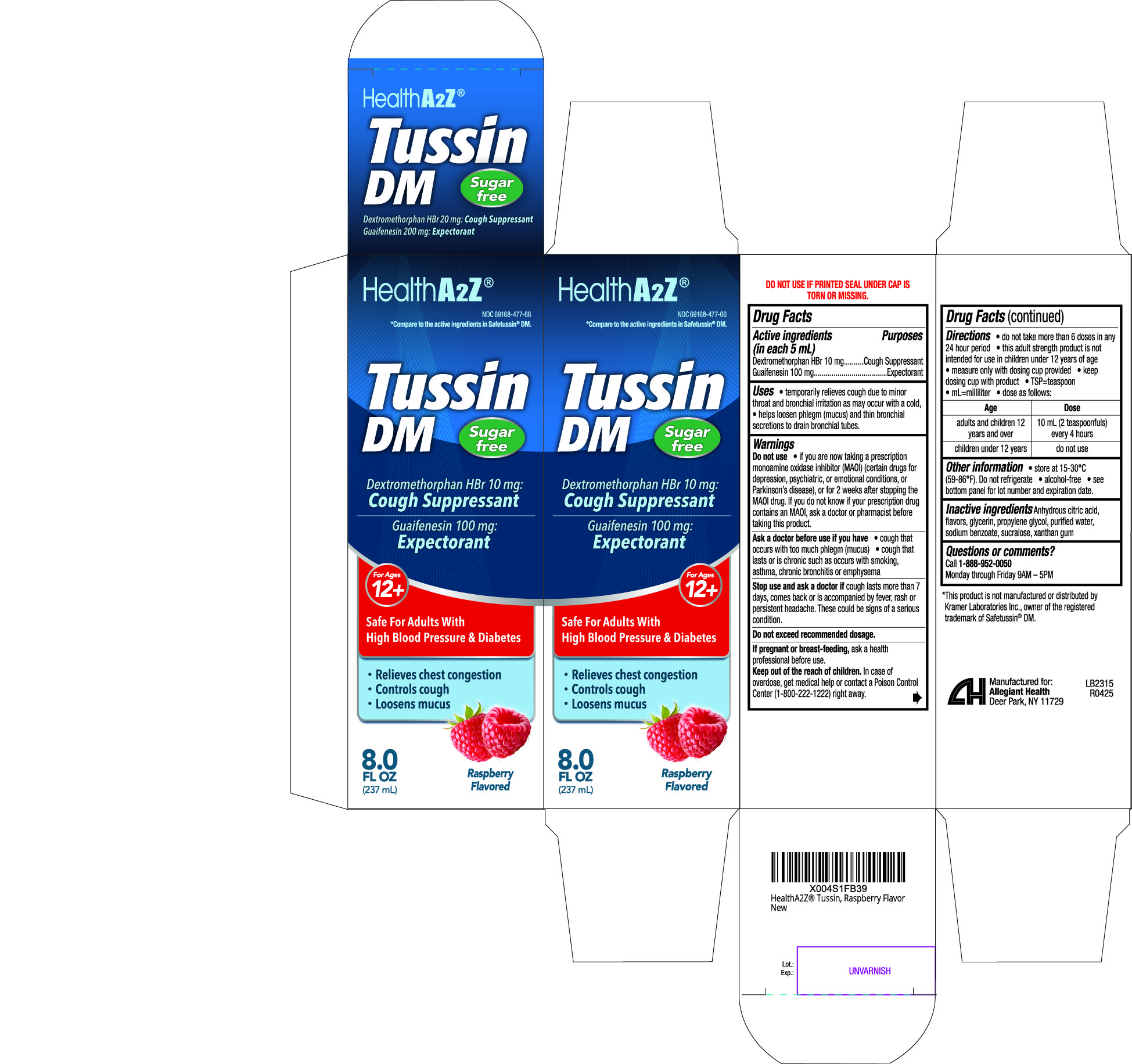 DRUG LABEL: Tussin DM
NDC: 69168-477 | Form: LIQUID
Manufacturer: Allegiant Health
Category: otc | Type: HUMAN OTC DRUG LABEL
Date: 20250723

ACTIVE INGREDIENTS: DEXTROMETHORPHAN HYDROBROMIDE 10 mg/5 mL; GUAIFENESIN 100 mg/5 mL
INACTIVE INGREDIENTS: ANHYDROUS CITRIC ACID; GLYCERIN; PROPYLENE GLYCOL; WATER; SODIUM BENZOATE; SUCRALOSE; XANTHAN GUM

477 - Tussin DM

Active ingredient(s)

Dextromethorphan HBr 10 mg
Guaifenesin 100 mg

(In each 5mL)

Purpose

Cough Suppressant
Expectorant

Use(s)

temporarily relieves cough due to minor throat and bronchial irritation as may occur with a cold

helps loosen phlegm (mucus) and thin bronchial secretions to drain bronchial tubes

Warnings

Do not use

if you are now taking a prescription monoamine oxidase inhibitor (MAOI) (certain drugs for
depression, psychiatric, or emotional conditions, or Parkinson’s disease), or for 2 weeks after stopping the
MAOI drug. If you do not know if your prescription drug contains an MAOI, ask a doctor or pharmacist before taking this product.

Ask a doctor before use if you

• cough that occurs with too much phlegm (mucus)

• cough that lasts or is chronic such as occurs with smoking, asthma, chronic bronchitis or emphysema

Stop use and ask a doctor if

cough lasts more than 7 days, comes back or is accompanied by fever, rash or persistent headache. These could be signs of a serious condition.

If pregnant or breastfeeding,

ask a health professional before use.

Keep out of reach of children

In case of overdose, get medical help or contact a Poison Control Center (1-800-222-1222) right away.

Directions

• do not take more than 6 doses in any 24 hour period

• this adult strength product is not intended for use in children under 12 years of age
• measure only with dosing cup provided

• keep dosing cup with product

• TSP=teaspoon • mL=milliliter • dose as follows:

Age | Dose
adults and children; 12 years and over | 10 mL (2 Teaspoonfuls) every 4 hours
children under 12 years | do not use

Other information

• store at 15-30°C (59-86°F). Do not refrigerate

• alcohol-free

• see bottom panel for lot number and expiration date.

DO NOT USE IF PRINTED SEAL UNDER CAP IS TORN OR MISSING.

Inactive ingredients

Anhydrous citric acid, flavors, glycerin, propylene glycol, purified water, sodium benzoate, sucralose, xanthan gum.

Questions/Comments

Call 1-888-952-0050 (Monday-Friday 9 AM – 5 PM EST)

Principal Display Panel

Tussin Label
Tussin Carton